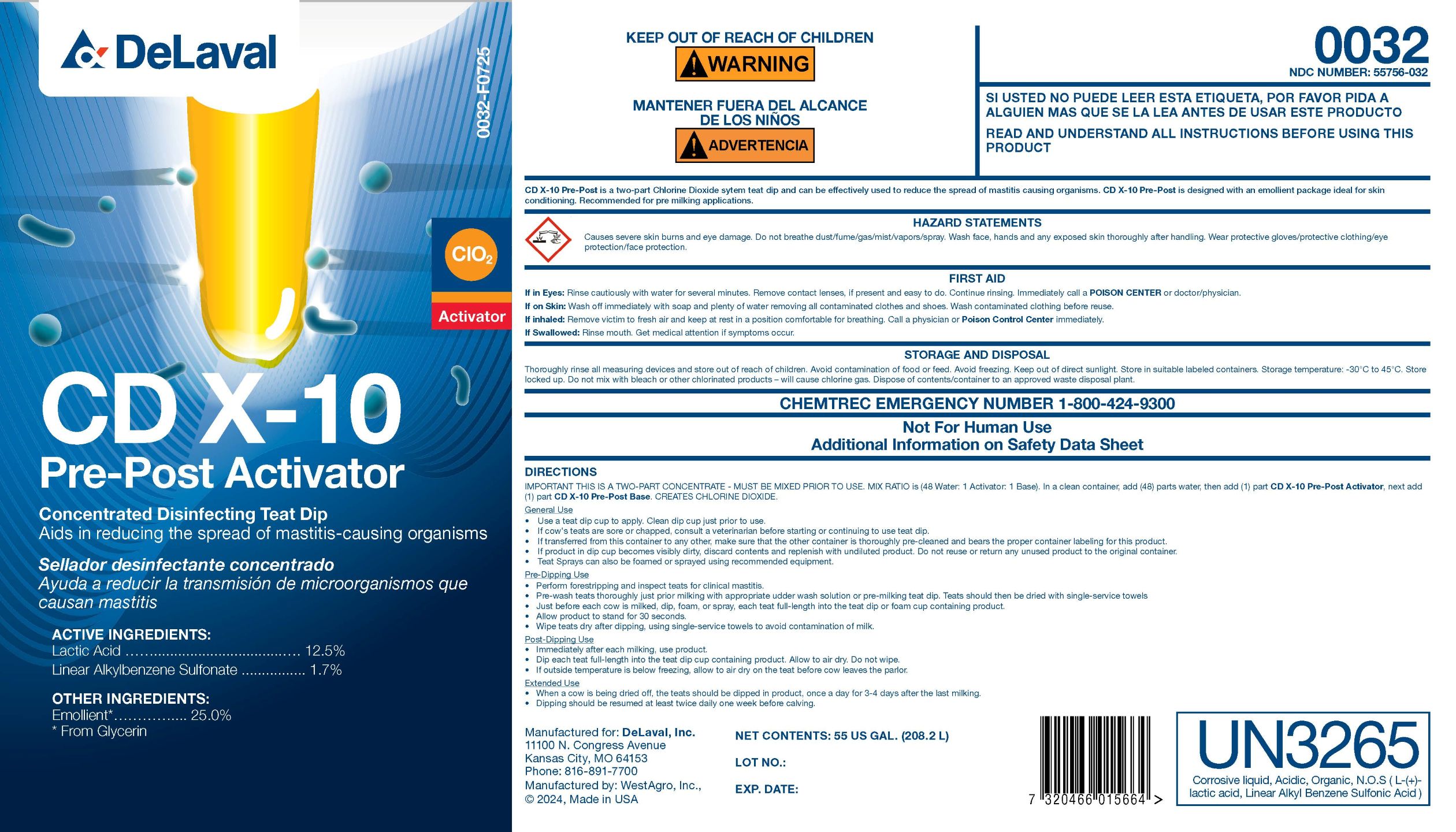 DRUG LABEL: CD X-10 Pre-Post Activator
NDC: 55756-032 | Form: CONCENTRATE
Manufacturer: DeLaval
Category: animal | Type: OTC ANIMAL DRUG LABEL
Date: 20251028

ACTIVE INGREDIENTS: LACTIC ACID 125 g/1 L; 2-PHENYLDODECANE-P-SULFONATE 17 g/1 L
INACTIVE INGREDIENTS: WATER; UREA; GLYCERIN; SODIUM C14-16 OLEFIN SULFONATE

CD X-10 Pre-Post Activator

PURPOSE

Concentrated Disinfecting Teat Dip

Aids in reducing the spread of mastitis-causing organisms

ACTIVE INGREDIENTS:

Lactic Acid ......................................... 12.5%

Linear Alkylbenzene Sulfonate ............... 1.7%

OTHER INGREDIENTS:

Emollient*....................25.0%

*From Glycerin

KEEP OUT OF REACH OF CHILDREN

! WARNING

WARNINGS

READ AND UNDERSTAND ALL INSTRUCTIONS BEFORE USING THIS PRODUCT

INDICATIONS AND USAGE

CD X-10 Pre-Post is a two-part Chlorine Dioxide system teat dip and can be effectively used to reduce the spread of mastitis causing organisms. CD X-10 Pre-Post is designed with an emollient package ideal for skin conditoning. Recommended for pre milking applications.

WARNINGS

HAZARD STATEMENTS
Causes severe skin burns and eye damage. Do not breathe dust/fume/gas/mist/vapors/spray. Wash face, hands, and any exposed skin thoroughly after handling. Wear protective gloves/protective clothing/eye protection/face protection.

UN3265: Corrosive liquid, Acidic, Organic, N.O.S. (L-(+)- lactic acid, Linear Alkyl Benzene Sulfonic Acid)

FIRST AID

If in Eyes: Rinse cautiously with water for several minutes. Remove contact lenses, if present and easy to do. Continue rinsing. Immediately call a POISON CENTER or doctor/physician.

If on Skin: Wash off immediately with soap and plenty of water removing all contaminated clothes and shoes. Wash contaminated clothing before reuse.

If inhaled: Remove victim to fresh air and keep at rest in a position comfortable for breathing. Call a physician or Poison Control Center immediately.

If Swallowed: Rinse mouth. Get medical attention if symptoms occur.

STORAGE AND DISPOSAL

Thoroughly rinse all measuring devices and store out of reach of children. Avoid contamination of food or feed. Avoid freezing. Keep out of direct sunlight. Store in suitable labeled containers. Storage temperature: -30°C to 45°C. Store locked up. Do not mix with bleach or other chlorinated products - will cause chlorine gas. Dispose of contents/container to an approved waste disposal plant.

CHEMTREC EMERGENCY NUMBER 1-800-424-9300

WARNINGS AND PRECAUTIONS

Not For Human Use

Additional Information on Safety Data sheet

DIRECTIONS

IMPORTANT THIS IS A TWO-PART CONCENTRATE - MUST BE MIXED PRIOR TO USE. MIX RATIO is (48 Water: 1 Activator: 1 Base). In a clean container, add (48) parts water, then add (1) part CD X-10 Pre-Post Activator, next add (1) part CD X-10 Pre-Post Base. CREATES CHLORINE DIOXIDE.

General Use

- Use a teat dip cup to apply. Clean dip cup just prior to use.
- If cow's teats are sore or chapped, consult a veterinarian before starting or continuing to use teat dip.
- If transferred from this container to any other, make sure that the other container is thorougly pre-cleaned and bears the proper container labeling for this product.
- If product in dip cup becomes visibly dirty, discard contents and replenish with undiluted product. Do not reuse or return any unused product to the original container.
- Teat Sprays can also be foamed or sprayed using recommended equipment.

Pre-Dipping Use

- Perform forestripping and inspect teats for clinical mastitis.
- Pre-Wash teats thoroughly just prior milking with appropriate udder wash solution or pre-milking teat dip. Teats should then be dried with single-service towels.
- Just before each cow is milked, dip, foam, or spray, each teat full-length into the teat dip or foam cup containing product.
- Allow product to stand for 30 seconds.
- Wipe teats dry after dipping, using single-service towels to avoid contamination of milk.

Post-Dipping Use

- Immediately after each milking, use product.
- Dip each teat full-length into the teat dip cup containing product. Allow to air dry. Do not wipe.
- If outside temperature is below freezing, allow to air dry on the teat before cow leaves the parlor.

Extended Use

- When a cow is being dried off, the teats should be dipped in product, once a day for 3-4 days after the last milking.
- Dipping should be resumed at least twice daily one week before calving.

NET CONTENTS: GAL. (L)

LOT NO.:

EXP. DATE:

Manufactured for: DeLaval, Inc.

11000 N. Congress Avenue

Kansas City, MO 64153

Phone: 816-891-7700

Manufactured by: WestAgro, Inc.,

© 2024, Made in USA